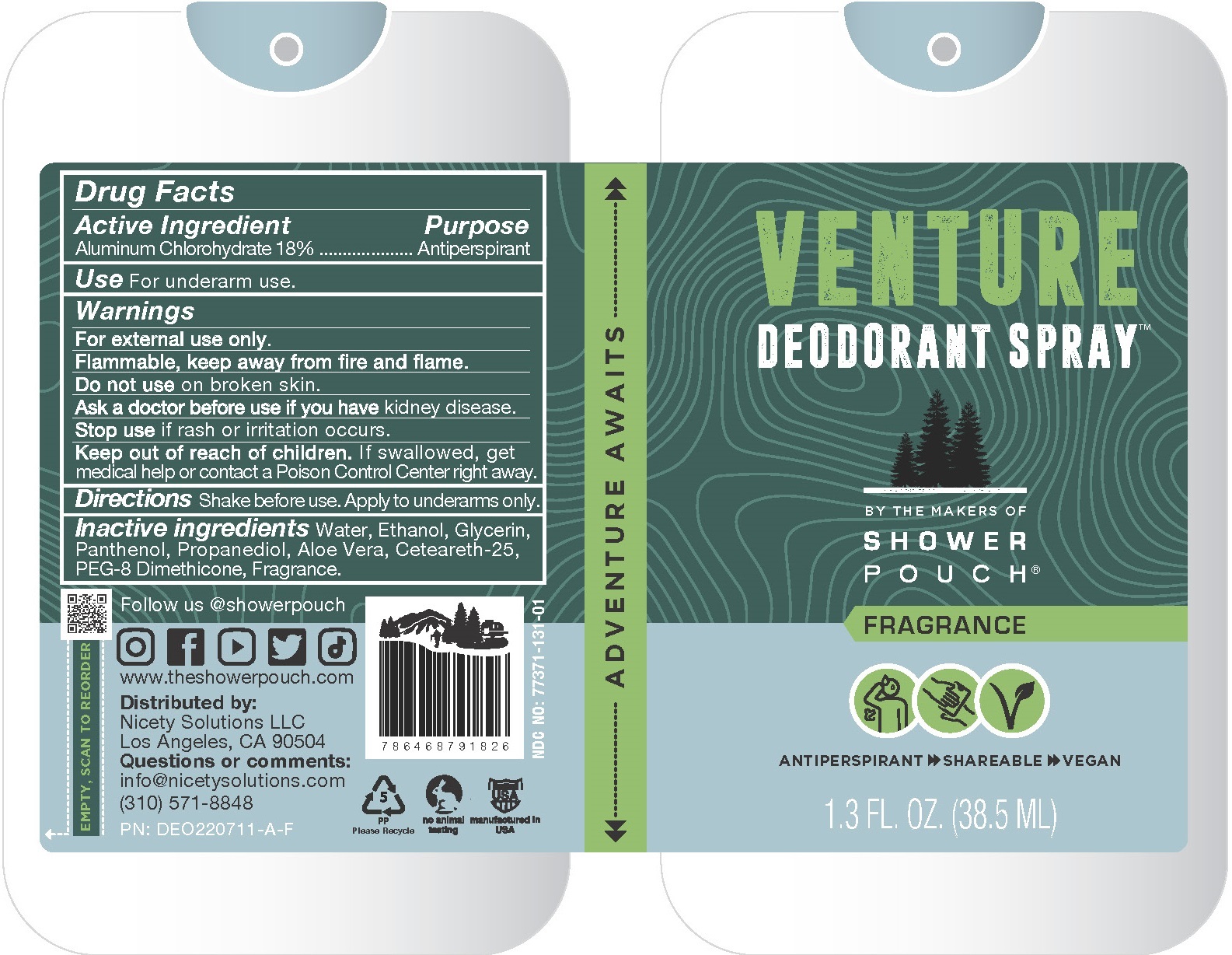 DRUG LABEL: Venture Antiperspirant Deodorant (Fragrance)
NDC: 77371-131 | Form: SPRAY
Manufacturer: NICETY SOLUTIONS LLC
Category: otc | Type: HUMAN OTC DRUG LABEL
Date: 20220714

ACTIVE INGREDIENTS: ALUMINUM CHLOROHYDRATE 15 g/100 mL
INACTIVE INGREDIENTS: WATER; ALCOHOL; ALOE VERA LEAF; PANTHENOL; GLYCERIN; PROPANEDIOL; CETEARETH-25; PEG-8 DIMETHICONE

Venture Antiperspirant Deodorant Fragrance

Active ingredient

Aluminum Chlorohydrate 18%

Purpose

Antiperspirant

Use

For underarm use to decrease wetness.

Warnings

For external use only

Flammable, keep away from fire and flame

Do not use

on broken skin

Ask a doctor before use if you have

kidney disease

Stop use

if rash or irritation occurs

Keep out of reach of children

If swallowed, get medical help or contact an Poison Control Center right away.

Directions

Shake before use. Apply to underarms only.

Inactive ingredients

Water, Ethanol, Glycerin, Panthenol, Propanediol, Aloe Vera, Ceteareth-25, PEG-8 Dimethicone, Fragrance

Label

Venture Deodorant

By the makers of Shower Pouch

Fragrance

Antiperspirant, Sharable, Vegan

1.3 fl oz [38.5 ml]